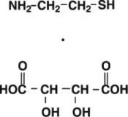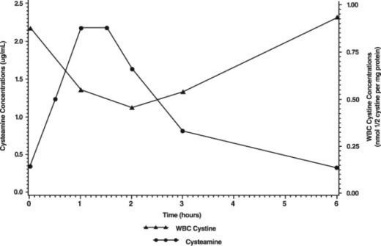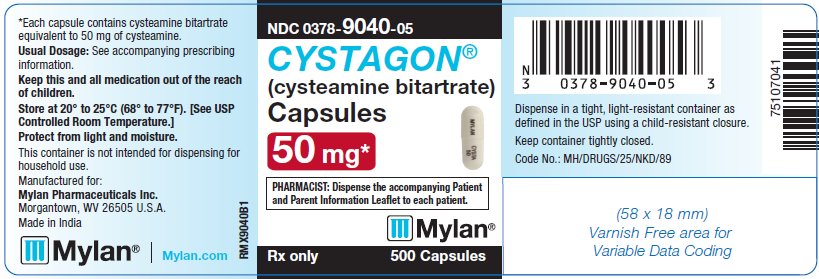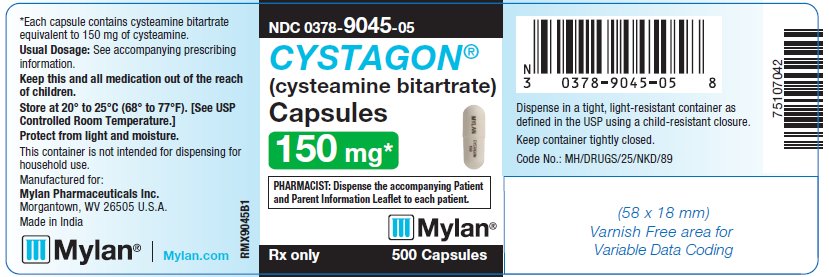 DRUG LABEL: Cystagon
NDC: 0378-9040 | Form: CAPSULE
Manufacturer: Mylan Pharmaceuticals Inc.
Category: prescription | Type: HUMAN PRESCRIPTION DRUG LABEL
Date: 20210816

ACTIVE INGREDIENTS: CYSTEAMINE BITARTRATE 50 mg/1 1
INACTIVE INGREDIENTS: AMMONIA; FERROSOFERRIC OXIDE; SILICON DIOXIDE; CROSCARMELLOSE SODIUM; GELATIN, UNSPECIFIED; MAGNESIUM STEARATE; MICROCRYSTALLINE CELLULOSE 112; STARCH, CORN; PROPYLENE GLYCOL; SODIUM LAURYL SULFATE; TITANIUM DIOXIDE; SHELLAC

DESCRIPTION

CYSTAGON® (cysteamine bitartrate) Capsules for oral administration, contain cysteamine bitartrate, a cystine depleting agent which lowers the cystine content of cells in patients with cystinosis, an inherited defect of lysosomal transport. CYSTAGON® is the bitartrate salt of cysteamine, an aminothiol, beta-mercaptoethylamine. Cysteamine bitartrate is a highly water soluble white powder with a molecular weight of 227 and the molecular formula C2H7NS • C4H6O6. It has the following chemical structure:

Each CYSTAGON® Capsule contains 50 mg or 150 mg of cysteamine free base as cysteamine bitartrate. CYSTAGON® Capsules contain the following inactive ingredients: ammonium hydroxide, black iron oxide, colloidal silicon dioxide, croscarmellose sodium, gelatin, magnesium stearate, microcrystalline cellulose, pharmaceutical glaze, pregelatinized starch, propylene glycol, sodium lauryl sulfate and titanium dioxide.

CLINICAL PHARMACOLOGY

Mechanism of Action

Cystinosis is an autosomal recessive inborn error of metabolism in which the transport of cystine out of lysosomes is abnormal; in the nephropathic form, accumulation of cystine and formation of crystals damage various organs, especially the kidney, leading to renal tubular Fanconi Syndrome and progressive glomerular failure, with end stage renal failure by the end of the first decade of life. In four studies of cystinosis patients before cysteamine was available, renal death (need for transplant or dialysis) occurred at median age of less than 10 years. Patients with cystinosis also experience growth failure, rickets, and photophobia due to cystine deposits in the cornea. With time most organs are damaged, including the retina, muscles and central nervous system.

Cysteamine is an aminothiol that participates within lysosomes in a thiol-disulfide interchange reaction converting cystine into cysteine and cysteine-cysteamine mixed disulfide, both of which can exit the lysosome in patients with cystinosis.

Pharmacokinetics and Pharmacodynamics

Normal individuals and persons heterozygous for cystinosis have white cell cystine levels of < 0.2 and usually below 1 nmol/½ cystine/mg protein, respectively. Individuals with nephropathic cystinosis have elevations of white cell cystine above 2 nmol/½ cystine/mg protein. White cell cystine is monitored in these patients to determine adequacy of dosing, levels being measured 5 to 6 hours after dosing. In the Long-Term Study (see Clinical Trials, below) entry white cell cystine levels were 3.73 nmol/½ cystine/mg protein (range 0.13 to 19.80 nmol/½ cystine/mg protein) and were maintained close to 1 nmol/½ cystine/mg protein with a cysteamine dose range of 1.3 to 1.95 g/m^2/day. After administration of cysteamine HCl, leukocyte cystine levels fall, with minimum levels at approximately 1 hour.

Because cysteamine HCl has an unpleasant taste and odor, other formulations have been developed, including phosphocysteamine, the phosphorothioester of cysteamine that is rapidly converted to cysteamine in the gut, and cysteamine bitartrate (CYSTAGON®). Cysteamine bitartrate has been shown in a transfer study in 8 patients to maintain white cell cystine levels below 1 nmol/½ cystine/mg protein when substituted for cysteamine HCl or phosphocysteamine. Total cysteamine levels 2 and 6 hours post-dosing were higher after cysteamine bitartrate than for the solutions.

The pharmacokinetics and pharmacodynamics of CYSTAGON® were studied in eleven pediatric patients with nephropathic cystinosis who received 225 to 550 mg of cysteamine bitartrate every 6 hours daily for more than one year. Following repeated oral administration of 225 to 550 mg cysteamine bitartrate, the mean time to maximum plasma concentration (Tmax) occurred at about 1.4 hours post dose with mean steady-state peak plasma concentration (Cmax) and area under the concentration-time curve (AUC) of 2.6 µg/mL and 6.3 µg∙hr/mL, respectively. The apparent volume of distribution and apparent plasma clearance of cysteamine were 156 L and 1.2 L/min, respectively.

Cysteamine was moderately bound to human plasma proteins, predominantly to albumin, with mean protein binding of about 52%. Plasma protein binding was independent of concentration over the concentration range achieved clinically with the recommended doses.

The pharmacodynamic response increased with the plasma cysteamine concentration, with maximum response occurring approximately 1.8 hours post dose with an average reduction of white cell cystine concentration of about 0.46 nmol/½ cystine/mg protein and returning to baseline level 6 hours post dose.

The mean white cell cystine concentration and mean cysteamine plasma concentration-time profile is shown below:

Most clinical data have been developed using cysteamine HCl or phosphocysteamine solutions. In all discussions that follow, administered amounts of various cysteamine salts will be expressed as amounts of cysteamine free base.

Clinical Studies

There are approximately 200 pre-transplant cystinosis patients in the United States with nephropathic cystinosis and clinical studies have included almost all of them, in addition to about 40 studied in the United Kingdom. For all patients, mean age at entry into studies was just under 4 years. Patients were approximately equally divided between genders and about 85% were white, 9% were black, and 3% were hispanic.

The National Collaborative Cysteamine Study (NCCS) treated 94 children (mainly from the United States) with nephropathic cystinosis with increasing doses of cysteamine HCl (mean dose 54 mg/kg/day) to attain white cell cystine levels of less than 2 nmol/½ cystine/mg protein 5 to 6 hours post-dose, and compared their outcome with an historical control group of 17 children who had been in the placebo group of a randomized placebo-controlled trial of ascorbic acid. Cysteamine treated patients had been diagnosed at a mean age of 22 months and were a mean age of 46 months old at study entry; placebo patients had been diagnosed at about 29 months and were a mean age of about 52 months old at study entry. The principal measures of effectiveness were serum creatinine and calculated creatinine clearance and growth (height).

The average median white cell cystine level attained during treatment in the NCCS was 1.7 ± 0.2 nmol/½ cystine/mg protein. There were 70 cysteamine patients with baseline serum creatinine less than 2 mg/dL who were followed for at least a year and 17 placebo patients. Twelve of the 94 cysteamine treated patients required early dialysis or renal transplant. Median follow-up of cysteamine patients was over 32 months and 20% were followed more than 5 years. For the placebo group median follow-up was 20 months and only one was followed more than 24 months. Among cysteamine patients glomerular function was maintained over time despite the longer period of treatment and follow-up. Placebo treated patients, in contrast, experienced a gradual rise in serum creatinine. Height, corrected for age, was compared for treated patients with the height, at the various ages patients appeared, of the 143 patients initially screened for inclusion in the NCCS. Patients on treatment maintained growth (did not show increasing growth failure compared to normals) although growth velocity did not increase enough to allow patients to catch up to age norms. Renal tubular function was not affected by treatment.

Calculated creatinine clearances were evaluated for two groups of children, one with poor white cell cystine depletion and one with good white cell cystine depletion as shown in Table I. The final mean creatinine clearance of the good depletion group was 20.8 ml/min/1.73 m^2 greater than the mean for the poor depletion group, despite the older mean age of the good depletion group.

TABLE 1: CREATININE CLEARANCE CHANGES BY WHITE CELL CYSTINE DEPLETION
 | Age (years) |  | Creatinine Clearance (ml/min/1.73m^2)
 | Initial | Final | Initial | Final
Poor Depletion [Median leukocyte cystine levels were over 3 nmol/½ cystine/mg protein or were not measured at least 2 times per year. Patients did receive cysteamine for at least 1 year.] (n = 18) | 4.2 ± 1.8 | 6.5 ± 0.5 | 33.6 ± 17.0 | 29.7 ± 5.4
Good Depletion [Median leukocyte cystine levels were less than 1 nmol/½ cystine/mg protein and received cysteamine for at least 1 year.] (n = 19) | 3.3 ± 2.2 | 7.2 ± 0.7 | 44.3 ± 15.0 | 50.5 ± 5.1
(95% confidence limits on difference between final creatinine clearances, 6.1 and 35.5 ml/min/1.73m^2, despite older mean age of good depletion group.)

The Long Term Study, initiated in 1988, utilized both cysteamine HCl and phosphocysteamine (patient’s choice) in 46 patients who had completed the NCCS (averaging 6.5 years of treatment) and 93 new patients. Patients had cystinosis diagnosed by elevated white cell cystine (mean 3.63 nmol/½ cystine/mg). New patients and 46 continuing patients were required to have serum creatinine less than 3.0 mg/dL and 4.0 mg/dL, respectively. Patients were randomized to doses of 1.3 or 1.95 g/m^2/day and stratified according to whether the serum creatinine was above 1.2 mg/dL or not. Doses could be raised if white cell cystine levels were approximately 2 nmol/½ cystine/mg protein and lowered due to intolerance.

Mean doses were 1.27 g/m^2/day and 1.87 g/m^2/day in the two groups and white cell cystine levels averaged 1.72 ± 1.65 nmol/½ cystine/mg protein and 1.86 ± 0.92 nmol/½ cystine/mg protein in the 1.3 and 1.95 g/m^2/day groups, respectively. In new patients, a group similar in age to the NCCS group, serum creatinine was essentially unchanged over the period of follow-up (about half of the patients were followed for 24 months) and phosphocysteamine and cysteamine HCl had similar effects. The long-term follow-up group, about nine years old on average at entry, stayed in the study (almost 80% were followed at least 2 years) and had essentially no change in renal function. In four studies of untreated cystinosis, renal death (need for transplant or dialysis) occurred at median age of less than 10 years. Both groups maintained height (although they did not catch up from baseline). There was no apparent difference between the two doses.

INDICATIONS AND USAGE

CYSTAGON® is indicated for the management of nephropathic cystinosis in children and adults.

CONTRAINDICATIONS

CYSTAGON® is contraindicated in patients who have developed hypersensitivity to it or to cysteamine or penicillamine.

WARNINGS

If a skin rash develops, CYSTAGON® should be withheld until the rash clears. CYSTAGON® may be restarted at a lower dose under close supervision, then slowly titrated to the therapeutic dose. If a severe skin rash develops such as erythema multiforme bullosa or toxic epidermal necrolysis, CYSTAGON® should not be readministered.

CNS symptoms such as seizures, lethargy, somnolence, depression, and encephalopathy have been associated with cysteamine. If CNS symptoms develop, the patient should be carefully evaluated and the dose adjusted as necessary. Neurological complications have been described in some cystinotic patients not on cysteamine treatment. This may be a manifestation of the primary disorder. Patients should not engage in hazardous activities until the effects of CYSTAGON® on mental performance are known.

Gastrointestinal ulceration and bleeding have been reported in patients receiving cysteamine bitartrate. Physicians should remain alert for signs of ulceration and bleeding and should inform patients and/or guardians about the signs and symptoms of serious G.I. toxicity and what steps to take if they occur.

Post-marketing reports include one report of interstitial nephritis with early renal failure. A causal relationship between this event and cysteamine bitartrate therapy has not been established.

PRECAUTIONS

General

Gastrointestinal tract symptoms including nausea, vomiting, anorexia and abdominal pain have been associated with cysteamine, sometimes severe. In addition, gastrointestinal ulceration and bleeding have been reported in patients on cysteamine therapy. If these develop, therapy may have to be interrupted and the dose adjusted. A cysteamine dose of 1.95 grams/m^2/day (approximately 80 to 90 mg/kg/day) was associated with an increased number of withdrawals from treatment due to intolerance and an increased incidence of adverse events.

Cysteamine has occasionally been associated with reversible leukopenia and abnormal liver function studies. Therefore, blood counts and liver function studies should be monitored.

There have been reports of benign intracranial hypertension (or pseudotumor cerebri; PTC) and/or papilledema associated with CYSTAGON® treatment that has resolved with the addition of diuretic therapy. PTC may be more common in cystinotic patients because of concurrent medication and renal transplantation. Although a causal relationship of PTC to CYSTAGON® has not been established, physicians should monitor patients receiving CYSTAGON® for this condition. Physicians should instruct patients to report any of the following symptoms: headache, tinnitus, dizziness, nausea, diplopia, blurry vision, loss of vision, pain behind the eye or pain with eye movement. A periodic eye examination is needed to identify this condition early and timely treatment should be provided when it occurs to prevent vision loss.

There have been reports of serious skin lesions in patients treated with high doses of CYSTAGON® or other cysteamine salts that have responded to cysteamine dose reduction. These skin lesions are purplish hemorrhagic lesions over the elbow area on both arms and have been described as molluscoid pseudotumors. Skin striae, bone lesions (that have been described as osteopenia, compression fractures, scoliosis and genu valgum) along with leg pain and joint hyperextension may also be present. One patient with serious skin lesions subsequently died of acute cerebral ischemia with marked vasculopathy. Physicians should routinely monitor the skin and bones of patients receiving CYSTAGON®. If similar skin or bone abnormalities appear, the dose of CYSTAGON® should be reduced.

Information for Patients and Parents and/or Guardians

See attached information for patients and parents and/or guardians.

Laboratory Tests

Leukocyte cystine measurements are useful to determine adequate dosage and compliance. When measured 5 to 6 hours after CYSTAGON® administration, the goal should be a level < 1 nmol/½ cystine/mg protein. In some patients with poorer tolerability for CYSTAGON®, patients may still receive benefit with a white cell cystine level of less than 2 nmol/½ cystine/mg protein. Measurements should be done every three months, more frequently when patients are transferred from cysteamine hydrochloride or phosphocysteamine solutions to CYSTAGON®.

Physicians should follow patients for signs and symptoms of gastrointestinal ulceration and bleeding, and should inform patients and/or guardians of the importance of this follow-up.

Drug Interactions

None have been described. CYSTAGON® can be administered with electrolyte and mineral replacements necessary for management of the Fanconi Syndrome as well as vitamin D and thyroid hormone.

Carcinogenesis, Mutagenesis, Impairment of Fertility

Cysteamine has not been tested for its carcinogenic potential in long-term animal studies.

Cysteamine was not mutagenic in the Ames test. It produced a negative response in an in-vitro sister chromatid exchange assay in human lymphocytes, but a positive response in a similar assay in hamster ovarian cells.

Repeat breeding reproduction studies were conducted in male and female rats. Cysteamine was found to have no effect on fertility and reproductive performance at an oral dose of 75 mg/kg/day (450 mg/m^2/day, 0.4 times the recommended human dose based on body surface area). At an oral dose of 375 mg/kg/day (2,250 mg/m^2/day, 1.7 times the recommended human dose based on body surface area), it reduced the fertility of the adult rats and the survival of their offspring.

Pregnancy

Teratology studies have been performed in rats at oral doses in a range of 37.5 to 150 mg/kg/day (about 0.2 to 0.7 times the recommended human maintenance dose on a body surface basis) and have revealed cysteamine bitartrate to be teratogenic and fetotoxic. Observed teratogenic findings were cleft palate, Kyphosis, heart ventricular septal defects, microcephaly and exencephaly. There are no adequate and well-controlled studies in pregnant women. CYSTAGON® should be used during pregnancy only if the potential benefit justifies the potential risk to the fetus.

Nursing Mothers

It is not known whether cysteamine is excreted in human milk. Because many drugs are excreted in human milk and because of the manifested potential of cysteamine for developmental toxicity in suckling rat pups when it was administered to their lactating mothers at an oral dose of 375 mg/kg/day (2,250 mg/m^2/day, 1.7 times the recommended human dose based on body surface area), a decision should be made whether to discontinue nursing or to discontinue the drug, taking into account the importance of the drug to the mother.

Pediatric Use

The safety and effectiveness of CYSTAGON® for cystinotic children have been established. Cysteamine therapy should be initiated as soon as the diagnosis of nephropathic cystinosis has been confirmed.

ADVERSE REACTIONS

In three clinical trials, cysteamine or phosphocysteamine have been administered to 246 children with cystinosis. Causality of side effects is sometimes difficult to determine because adverse effects may result from the underlying disease.

The most frequent adverse reactions seen involve the gastrointestinal and central nervous systems. These are especially prominent at the initiation of cysteamine therapy. Temporarily suspending treatment, then gradual re-introduction may be effective in improving tolerance.

Adverse reactions were not collected systematically in the NCCS, but were often listed by investigators. The following rates may therefore be underestimated. The most common events (> 5%) were vomiting 35%, anorexia 31%, fever 22%, diarrhea 16%, lethargy 11%, and rash 7%.

Less common adverse events are:

Body as a whole: Dehydration.

Cardiovascular: Hypertension.

Digestive: Nausea, bad breath, abdominal pain, dyspepsia, constipation, gastroenteritis, duodenitis, gastrointestinal ulceration and bleeding.

Central Nervous System: Somnolence, encephalopathy, headache, seizures, ataxia, confusion, tremor, hyperkinesia, decreasing hearing, dizziness, jitteriness.

Psychiatric: Nervousness, abnormal thinking, depression, emotional lability, hallucinations, nightmares.

Integumentary: Urticaria.

Urogenital: Interstitial nephritis, renal failure (see WARNINGS).

Clinical Laboratory: Abnormal liver function, anemia, leukopenia.

Adverse reactions or intolerance leading to cessation of treatment occurred in 8% of patients in the U.S. Studies.

Withdrawals due to intolerance, vomiting associated with medication, anorexia, lethargy, and fever appeared dose related, occurring more frequently in those patients receiving 1.95 grams/m^2/day as compared to 1.30 grams/m^2/day.

 | Dose in Grams/m^2/day
 | 1.30 (n = 42) % | 1.95 (n = 51) %
Vomiting Considered Related to Medicine | 31 | 67
Anorexia | 33 | 51
Lethargy | 17 | 27
Diarrhea | 31 | 31
Fever | 28 | 45

Sudden deaths have been reported in this disease state.

Post-marketing surveillance

Benign intracranial hypertension (or pseudotumor cerebri; PTC) with papilledema; skin lesions, molluscoid pseudotumors, skin striae, skin fragility; joint hyperextension, leg pain, genu valgum, osteopenia, compression fracture and scoliosis have been reported (see PRECAUTIONS).

DRUG ABUSE AND DEPENDENCE

CYSTAGON® has not been associated with abuse potential, psychological or physical dependence in humans.

OVERDOSAGE

A single oral dose of cysteamine at 660 mg/kg was lethal to rats. Symptoms of acute toxicity were reduction of motor activity and generalized hemorrhage in gastrointestinal tract and kidneys.

Two cases of human overdosage have been reported. In one case, the patient immediately vomited the drug and did not develop any symptoms. The second incident involved an accidental ingestion of a 200 to 250 mg/kg dose by a healthy 13 month old child. Vomiting and dehydration were experienced. The child was hospitalized and fluids were administered. A full recovery was made. Should overdose occur, the respiratory and cardiovascular systems should be supported appropriately. No specific antidote is known. Hemodialysis may be considered since cysteamine is poorly bound to plasma proteins.

DOSAGE AND ADMINISTRATION

For the management of nephropathic cystinosis, cysteamine therapy should be initiated promptly once the diagnosis is confirmed (i.e., increased white cell cystine).

New patients should be started on ¼ to 1/6 of the maintenance dose of CYSTAGON®. The dose should then be raised gradually over four to six weeks to avoid intolerance.

The recommended CYSTAGON® maintenance dose for children up to age 12 years is 1.30 grams/m^2/day of the free base, given in four divided doses. Intact CYSTAGON® capsules should not be administered to children under the age of approximately six years due to the risk of aspiration. CYSTAGON® capsules may be administered to children under the age of approximately six years by sprinkling the capsule contents over food. Patients over age 12 and over 110 pounds weight should receive 2.0 grams/day, divided four times daily.

If a dose is missed, it should be taken as soon as possible. If it is within two hours of the next dose, skip the missed dose and go back to the regular dosing schedule. Do not double dose.

When CYSTAGON® is well tolerated, the goal of therapy is to keep leukocyte cystine levels below 1 nmol/½ cystine/mg protein five to six hours following administration of CYSTAGON®. Patients with poorer tolerability still receive significant benefit if white cell cystine levels are below 2 nmol/½ cystine/mg protein. The CYSTAGON® dose can be increased to a maximum of 1.95 grams/m^2/day to achieve this level. The dose of 1.95 grams/m^2/day has been associated with an increased rate of withdrawal from treatment due to intolerance and an increased incidence of adverse events.

Cystinotic patients taking cysteamine hydrochloride or phosphocysteamine solutions may be transferred to equimolar doses of CYSTAGON® capsules.

The recommended maintenance dose of 1.30 grams/m^2/day can be approximated by administering CYSTAGON® according to the following table, which takes surface area as well as weight into consideration.

Weight in Pounds | mg of Cysteamine Free Base Every 6 Hours
0 - 10 | 100
11 - 20 | 150
21 - 30 | 200
31 - 40 | 250
41 - 50 | 300
51 - 70 | 350
71 - 90 | 400
91 - 110 | 450
> 110 | 500

Patients over age 12 and over 110 pounds should receive 2.0 grams/day given in four divided doses as a starting maintenance dose. This dose should be reached after 4 to 6 weeks of incremental dosage increases as stated above. The dose should be raised if the leukocyte cystine level remains > 2 nmol/½ cystine/mg/protein.

Leukocyte cystine measurements, taken 5 to 6 hours after dose administration, are recommended for new patients after the maintenance dose is achieved. Patients being transferred from cysteamine hydrochloride or phosphocysteamine solutions to capsules should have their white cell cystine levels measured in 2 weeks, and thereafter every 3 months to assess optimal dosage as described above.

If CYSTAGON® is poorly tolerated initially due to gastrointestinal tract symptoms or transient skin rashes, therapy should be temporarily stopped, then re-instituted at a lower dose and gradually increased to the proper dose.

HOW SUPPLIED

CYSTAGON® (cysteamine bitartrate) Capsules are hard gelatin capsules which provide 50 mg or 150 mg of cysteamine free base as cysteamine bitartrate:

CYSTAGON® Capsules, 50 mg are white, opaque capsules printed with CYSTA 50 on the body and MYLAN on the cap. They are available as follows:

NDC 0378-9040-05
bottles of 500 capsules

CYSTAGON® Capsules, 150 mg are white, opaque capsules printed with CYSTAGON 150 on the body and MYLAN on the cap. They are available as follows:

NDC 0378-9045-05
bottles of 500 capsules

Store at 20° to 25°C (68° to 77°F). [See USP Controlled Room Temperature.]

Protect from light and moisture.

Dispense in a tight, light-resistant container as defined in the USP using a child-resistant closure.

PHARMACIST: Detach Patient Information Leaflet at each perforation and give leaflet to patient.

The following information is available for patients and/or guardians in the patient leaflet.

Patient and Parent Information About

CYSTAGON® (SIS-ta-gon)
(cysteamine bitartrate)
Capsules

Read the Patient Information that comes with CYSTAGON® before you or your child starts taking it and each time you get a refill. There may be new information. This leaflet does not take the place of talking with your doctor about your or your child’s medical condition or treatment.

What is CYSTAGON®?

CYSTAGON® is a medicine used to manage a medical condition called nephropathic cystinosis, in children and adults.

Nephropathic cystinosis is a rare inherited condition which causes the build up of a protein building block called cystine in the kidneys. The build up of cystine causes kidney problems. These kidney problems cause the body to lose too much sugar (glucose), proteins, and electrolytes. Cystinosis may lead to slow body growth, weak bones and worsening kidney failure.

Who should not take CYSTAGON®?

Do not take CYSTAGON® if you or your child is allergic to any of the ingredients in it, other products containing cysteamine, or penicillamine. See the end of this leaflet for a complete list of ingredients in CYSTAGON®.

What should I tell my or my child’s doctor before taking CYSTAGON®?

Tell your doctor about all of your medical conditions, including if you or your child:

- have had an allergic reaction to a medicine containing cysteamine in the past.
- have a skin rash or any bone problems.
- have a history of seizures, exhaustion, depression or other nervous system problems.
- have or have had stomach or intestinal problems including ulcers or bleeding.
- have liver or blood problems.
- are pregnant or plan to become pregnant. It is not known whether CYSTAGON® may harm your unborn baby. Do not take CYSTAGON® during pregnancy unless you and your doctor decide that the possible benefit of taking CYSTAGON® is more important than the risk to an unborn baby.
- It is not known if CYSTAGON® will pass into breast milk. You and your doctor should decide whether to stop nursing or to stop taking the medicine.

Tell your doctor about all of the medicines that you or your child takes, including prescription and non-prescription medicines, vitamins, and herbal supplements.

Know the medicines you or your child takes. Keep a list of your or your child’s medicines and show it to your or your child’s doctor and pharmacist when you get a new medicine.

How should CYSTAGON® be taken ?

- Take CYSTAGON® exactly as prescribed. Do not increase or decrease the amount of medicine without your doctor’s approval.
- If you or your child misses a dose of medicine, it should be taken as soon as possible. If it is within two hours of the next dose, skip the missed dose and go back to the regular dosing schedule. Do not double dose.
- If you or your child takes too much CYSTAGON®, call your doctor or Poison Control Center, or go to the nearest hospital emergency room right away.
- Do not give CYSTAGON® capsules to children under six years of age. They may not be able to swallow them and may choke. For children under six years of age, the capsule may be opened and the contents sprinkled on food. Talk to your doctor for complete directions.
- Your doctor will arrange for regular blood tests to be done to measure the amount of cystine inside white blood cells. This will help to determine the correct dose of CYSTAGON®. Regular blood and urine tests will also be done to measure the levels of the body’s important electrolytes. This will help your doctor to correctly adjust the doses of these supplements.
- Your doctor may also want to do certain tests to find out if unwanted effects are occurring. The tests are very important because serious side effects, including ulcers or bleeding in the stomach and intestines (digestive tract), can occur.

What should I or my child avoid while taking CYSTAGON®?

CYSTAGON® may cause some people to become sleepy or less alert than they are normally. You or your child should not drive, operate machinery, or do other dangerous activities until you know how CYSTAGON® affects you.

What are the possible side effects of CYSTAGON®?

CYSTAGON® can cause serious side effects, including:

1. Skin rash. Tell your doctor right away if you or your child gets a skin rash. CYSTAGON® may need to be temporarily stopped until the rash goes away. If the rash is severe, your doctor may totally stop the CYSTAGON®.
2. Central nervous system symptoms: Some patients taking cysteamine have developed seizures, depression, and become too sleepy (excessive sleepiness). Tell your doctor if you or your child has these symptoms.
3. Stomach and intestinal (gastrointestinal) problems: Patients taking cysteamine have developed ulcers and bleeding. Tell your doctor right away if you or your child get stomach pain, nausea, vomiting, loss of appetite, or throw up blood.
4. Low white blood cell count and abnormal liver function on blood tests. Your doctor will monitor you or your child for this.
5. Benign intracranial hypertension, also called pseudotumor cerebri, has been reported. This is a condition where there is high pressure in the fluid around the brain. Tell your doctor right away if you or your child develop any of the following symptoms while taking CYSTAGON®: headache, buzzing or “whooshing” sound in the ear, dizziness, nausea, double vision, blurry vision, loss of vision, pain behind the eye or pain with eye movement. Your doctor will monitor you or your child with eye examinations to find and treat this problem early. This will help lessen the chance of loss of eyesight.
6. Skin lesions, bone lesions, and joint problems. Children treated with high doses of cysteamine may develop skin lesions. These include skin striae (which are like stretch marks), bone injuries (such as fractures), bone deformities, and joint problems. Examine your or your child’s skin while taking CYSTAGON®. Report any changes to your doctor. Your doctor will monitor you or your child for these problems.

The most common side effects of CYSTAGON® include:

- Vomiting
- Loss of Appetite
- Fever
- Diarrhea
- Drowsiness
- Rash

How should I store CYSTAGON®?

- Store CYSTAGON® in a dry place away from light.
- Store CYSTAGON® between 68° to 77°F (20° to 25°C).

Keep CYSTAGON® and all medicines out of the reach of children.

General Information about CYSTAGON®

Medicines are sometimes prescribed for conditions that are not mentioned in the patient leaflet. Do not use CYSTAGON® for a condition for which it was not prescribed. Do not give CYSTAGON® to other people, even if they have the same symptoms that you or your child have. It may harm them.

This patient information summarizes the most important information about CYSTAGON®. If you would like more information about CYSTAGON®, talk with your doctor. You can ask your doctor or pharmacist for information about CYSTAGON® that is written for health professionals. For more information call 1-877-446-3679.

What are the ingredients in CYSTAGON®?

Active ingredient: cysteamine free base as cysteamine bitartrate.

Inactive ingredients: ammonium hydroxide, black iron oxide, colloidal silicon dioxide, croscarmellose sodium, gelatin, magnesium stearate, microcrystalline cellulose, pharmaceutical glaze, pregelatinized starch, propylene glycol, sodium lauryl sulfate and titanium dioxide.

Manufactured for:
Mylan Pharmaceuticals Inc.
Morgantown, WV 26505 U.S.A.

Manufactured by:
Mylan Laboratories Limited
Hyderabad – 500 096, India

75082040

Revised: 8/2021
MX:CYST:R1p/MX:PL:CYST:R1p

PRINCIPAL DISPLAY PANEL - 50 mg

NDC 0378-9040-05

CYSTAGON®
(cysteamine bitartrate)
Capsules
50 mg*

PHARMACIST: Dispense the accompanying Patient
and Parent Information Leaflet to each patient.

Rx only 500 Capsules

*Each capsule contains cysteamine bitartrate
equivalent to 50 mg of cysteamine.

Usual Dosage: See accompanying prescribing
information.

Keep this and all medication out of the reach
of children.

Store at 20° to 25°C (68° to 77°F). [See USP
Controlled Room Temperature.]

Protect from light and moisture.

This container is not intended for dispensing for
household use.

Manufactured for:
Mylan Pharmaceuticals Inc.
Morgantown, WV 26505 U.S.A.

Made in India

Mylan.com

RMX9040B1

Dispense in a tight, light-resistant container as
defined in the USP using a child-resistant closure.

Keep container tightly closed.

Code No.: MH/DRUGS/25/NKD/89

PRINCIPAL DISPLAY PANEL - 150 mg

NDC 0378-9045-05

CYSTAGON®
(cysteamine bitartrate)
Capsules
150 mg*

PHARMACIST: Dispense the accompanying Patient
and Parent Information Leaflet to each patient.

Rx only 500 Capsules

*Each capsule contains cysteamine bitartrate
equivalent to 150 mg of cysteamine.

Usual Dosage: See accompanying prescribing
information.

Keep this and all medication out of the reach
of children.

Store at 20° to 25°C (68° to 77°F). [See USP
Controlled Room Temperature.]

Protect from light and moisture.

This container is not intended for dispensing for
household use.

Manufactured for:
Mylan Pharmaceuticals Inc.
Morgantown, WV 26505 U.S.A.

Made in India

Mylan.com

RMX9045B1

Dispense in a tight, light-resistant container as
defined in the USP using a child-resistant closure.

Keep container tightly closed.

Code No.: MH/DRUGS/25/NKD/89